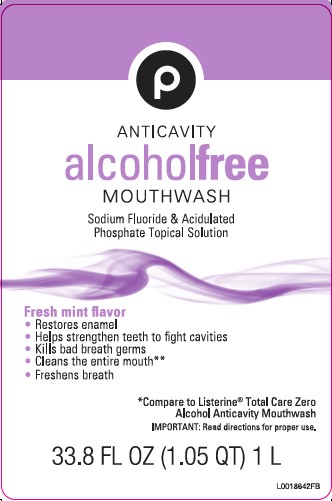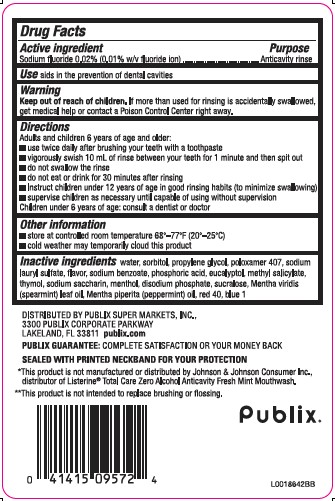 DRUG LABEL: Anticavity
NDC: 56062-971 | Form: RINSE
Manufacturer: Publix Super Markets, Inc.
Category: otc | Type: HUMAN OTC DRUG LABEL
Date: 20260205

ACTIVE INGREDIENTS: SODIUM FLUORIDE 0.02 mg/1 mL
INACTIVE INGREDIENTS: WATER; SORBITOL; PROPYLENE GLYCOL; POLOXAMER 407; SODIUM LAURYL SULFATE; SODIUM BENZOATE; PHOSPHORIC ACID; EUCALYPTOL; METHYL SALICYLATE; THYMOL; SACCHARIN SODIUM; MENTHOL, UNSPECIFIED FORM; SODIUM PHOSPHATE, DIBASIC, ANHYDROUS; SUCRALOSE; SPEARMINT OIL; PEPPERMINT OIL; FD&C RED NO. 40; FD&C BLUE NO. 1

Publix 971.001/971AB
Burn-Free Fluoride Anti-Cavity Mouthwash

Active Ingredient

Sodium fluoride 0.02% (0.01% w/v fluoride ion)

Purpose

Anticavity rinse

Use

aids in the prevention of dental cavities

Warning

for this product

Keep out of Reach of Children.

If more than used for rinsing is accidentally swallowed, get medical help or contact a Poison Control Center right away.

Directions

Adults and children 6 years of age and older:

- use twice daily after brushing your teeth with a toothpaste
- vigorously swish 10 mL (2 teaspoonfuls) of rinse between your teeth for 1 minute and then spit out.
- do not swallow the rinse
- do not eat or drink for 30 minutes after rinsing
- instruct children under 12 years of age in good rinsing habits (to minimize swallowing)
- supervise children as necessary until capable of using without supervision

Children under 6 years of age: consult a dentist or doctor

Other information

- store at controlled room temperature 68-77F (20-25C)
- cold weather may temporarily cloud this product

Inactive ingredients

water, sorbitol, propylene glycol, poloxamer 407, sodium lauryl sulfate, flavor, sodium benzoate, phosphoric acid, eucalyptol, methyl salicylate, thymol, sodium saccharin, menthol, disodium phosphate, sucralose, Mentha viridis (spearmint) leaf oil, Mentha piperita (peppermint) oil, red 40, blue 1

Disclaimers

*This product is not manufactured or distributed by Johnson & Johnson Healthcare Products, distributor of Listerine®Total Care Zero Alcohol Anticavity Fresh Mint Mouthwash.

**This product is not intended to replace brushing or flossing.

Adverse reactions section

DISTRIBUTED BY PUBLIX SUPER MARKETS, INC.

3300 PUBLIX CORPORATE PARKWAY

LAKELAND, FL 33811 publix.com

PUBLIX GUARNTEE: COMPLETE SATIFACTION OR YOUR MONEY BACK

SEALED WITH PRINTD NECKBND FOR YOUR PROTECTION

Publix

principal display panel

P

ANTICAVITY

alcoholfree

MOUTHWASH

Sodium Fluoride & Acidulated Phosphate Topical Solution

Fress mint flavor

- Restores enamel
- Helps strengthen teeth to fight cavities
- Kills bad breath germs
- Cleans the entire mouth**
- Freshens breath

*Compare to Listerine®Total Care Zero Alcohol Anticavity Mouthwash

IMPORTANT: Read directions for proper use.

33.8 FL OZ (1.05 QT) 1 L